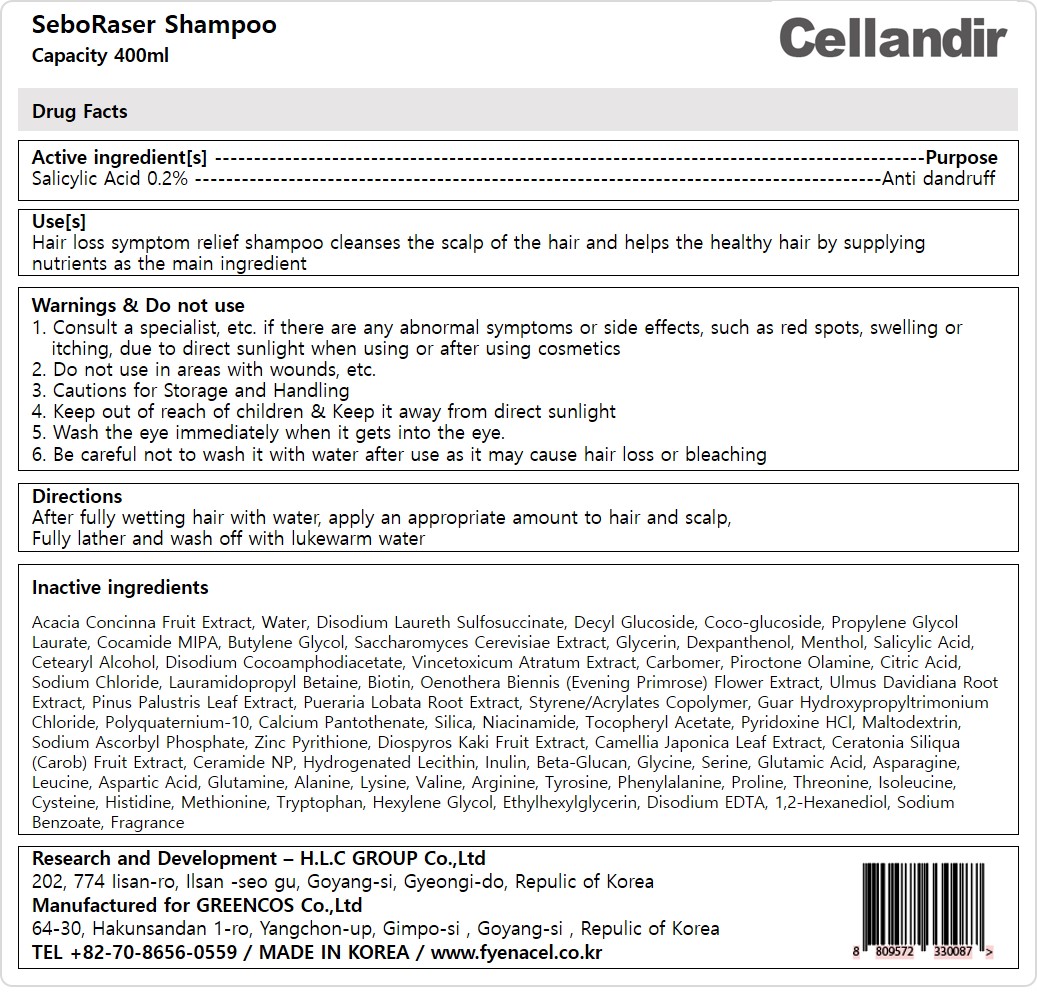 DRUG LABEL: SeboRaserShampoo
NDC: 81555-203 | Form: SHAMPOO
Manufacturer: H.L.C GROUP Co., ltd
Category: otc | Type: HUMAN OTC DRUG LABEL
Date: 20231124

ACTIVE INGREDIENTS: SALICYLIC ACID 0.2 mg/100 mL
INACTIVE INGREDIENTS: HYDROGENATED SOYBEAN LECITHIN; ACACIA CONCINNA FRUIT; DECYL GLUCOSIDE; COCO GLUCOSIDE; DISODIUM COCOAMPHODIACETATE; PIROCTONE OLAMINE; OENOTHERA BIENNIS FLOWER; STYRENE/ACRYLAMIDE COPOLYMER (MW 500000); ASPARAGINE; PYRIDOXINE HYDROCHLORIDE; HEXYLENE GLYCOL; ULMUS DAVIDIANA ROOT; SILICON DIOXIDE; TRYPTOPHAN; GLUTAMINE; CERAMIDE NP; CARBOMER HOMOPOLYMER, UNSPECIFIED TYPE; GLUTAMIC ACID; .ALPHA.-TOCOPHEROL ACETATE; CAROB; GLYCINE; MALTODEXTRIN; SERINE; LYSINE; ARGININE; PHENYLALANINE; VALINE; GUAR HYDROXYPROPYLTRIMONIUM CHLORIDE (1.7 SUBSTITUENTS PER SACCHARIDE); SODIUM CHLORIDE; PROPYLENE GLYCOL MONOLAURATE; NIACINAMIDE; LAURAMIDOPROPYL BETAINE; ETHYLHEXYLGLYCERIN; LEUCINE; 1,2-HEXANEDIOL; ASPARTIC ACID; ALANINE; TYROSINE; PROLINE; THREONINE; ISOLEUCINE; CYSTEINE; METHIONINE; HISTIDINE; WATER; GLYCERIN; BUTYLENE GLYCOL; CITRIC ACID MONOHYDRATE; EDETATE DISODIUM ANHYDROUS; SODIUM BENZOATE; MENTHOL, UNSPECIFIED FORM; DEXPANTHENOL; DISODIUM LAURETH SULFOSUCCINATE; COCO MONOISOPROPANOLAMIDE; PYRITHIONE ZINC; SACCHAROMYCES CEREVISIAE; PUERARIA MONTANA VAR. LOBATA ROOT; POLYQUATERNIUM-10 (1000 MPA.S AT 2%); CALCIUM PANTOTHENATE; SODIUM ASCORBYL PHOSPHATE; PERSIMMON; CAMELLIA JAPONICA LEAF; INULIN; YEAST .BETA.-D-GLUCAN; PINUS PALUSTRIS LEAF; CETOSTEARYL ALCOHOL; VINCETOXICUM ATRATUM WHOLE; BIOTIN

81555-203 SeboRaser Shampoo

Active ingredient[s]

SALICYLIC ACID 0.2%

Purpose

Anti dandruff

Use[s]

Hair loss symptom relief shampoo cleanses the scalp of the hair and helps the healthy hair by supplying nutrients as the main ingredient

Warnings

Consult a specialist, etc. if there are any abnormal symptoms or side effects, such as red spots, swelling or itching, due to direct sunlight when using or after using cosmetics

Cautions for Storage and Handling

Wash the eye immediately when it gets into your eye.

Be careful not to wash it with water after use as it may cause hair loss or bleaching

Do not use

in areas with wounds, etc.

Keep out of reach of children & Keep it away from direct sunlight

Directions

After fully wetting hair with water, apply an appropriate amount to hair and scalp,

Fully lather and wash off with lukewarm water

Inactive ingredients

Acacia Concinna Fruit Extract, Water, Disodium Laureth Sulfosuccinate, Decyl Glucoside, Coco-glucoside,

Propylene Glycol Laurate, Cocamide MIPA, Butylene Glycol, Saccharomyces Cerevisiae Extract, Glycerin, Dexpanthenol,

Menthol, Salicylic Acid, Cetearyl Alcohol, Disodium Cocoamphodiacetate, Vincetoxicum Atratum Extract, Carbomer, Piroctone Olamine, Citric Acid, Sodium Chloride, Lauramidopropyl Betaine, Biotin, Oenothera Biennis (Evening Primrose) Flower Extract, Ulmus Davidiana Root Extract, Pinus Palustris Leaf Extract, Pueraria Lobata Root Extract, Styrene/Acrylates Copolymer, Guar Hydroxypropyltrimonium Chloride, Polyquaternium-10, Calcium Pantothenate, Silica, Niacinamide, Tocopheryl Acetate, Pyridoxine HCl, Maltodextrin, Sodium Ascorbyl Phosphate, Zinc Pyrithione, Diospyros Kaki Fruit Extract, Camellia Japonica Leaf Extract, Ceratonia Siliqua (Carob) Fruit Extract, Ceramide NP, Hydrogenated Lecithin, Inulin, Beta-Glucan, Glycine, Serine, Glutamic Acid, Asparagine, Leucine, Aspartic Acid, Glutamine, Alanine, Lysine, Valine, Arginine, Tyrosine, Phenylalanine, Proline, Threonine, Isoleucine, Cysteine, Histidine, Methionine, Tryptophan, Hexylene Glycol, Ethylhexylglycerin, Disodium EDTA, 1,2-Hexanediol, Sodium Benzoate, Fragrance